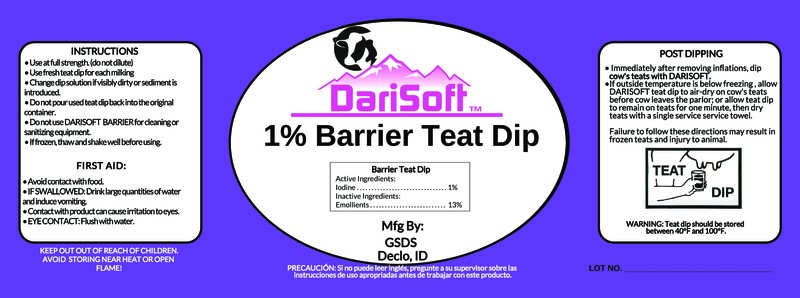 DRUG LABEL: DariSoft 1% Barrier Teat Dip
NDC: 86186-105 | Form: SOLUTION
Manufacturer: Gem State Dairy Supply
Category: animal | Type: OTC ANIMAL DRUG LABEL
Date: 20230924

ACTIVE INGREDIENTS: IODINE 10 g/1 L
INACTIVE INGREDIENTS: C9-11 PARETH-8; GLYCERIN; SODIUM HYDROXIDE; XANTHAN GUM

DariSoft™
1% Barrier Teat Dip

Active Ingredients:

Iodine.....................1%

PURPOSE

Barrier Teat Dip

INDICATIONS AND USAGE

INSTRUCTIONS

- Use at full strength (do not dilute)
- Use fresh teat dip for each milking
- Change dip solution if visibly dirty or sediment is introduced.
- Do not pour used teat dip back into the original container.
- Do not use DARISOFT BARRIER for cleaning or sanitizing equipment.
- If frozen, thaw and shake well before using.

POST DIPPING

- Immediately after removing inflations, dip cow's teats with DARISOFT.
- If outside temperature is below freezing, allow DARISOFT teat dip to air-dry on cow's teats before cow leaves the parlor; or allow teat dip to remain on teats for one minute, then dry teats with a single service towel.

Failure to follow these directions may result in frozen teats and injury to animal.

FIRST AID:

- Avoid contact with food.
- IF SWALLOWED: Drink large quantities of water and induce vomiting.
- Contact with product can cause irritation to eyes.
- EYE CONTACT: Flush with water.

KEEP OUT OF REACH OF CHILDREN

WARNINGS

WARNING: Teat dip should be stored between 40°F and 100°F.

AVOID STORING NEAR HEAT OR OPEN FLAME!

Inactive Ingredients:

Emollients.......................13%

PACKAGE LABEL

Add image transcription here...